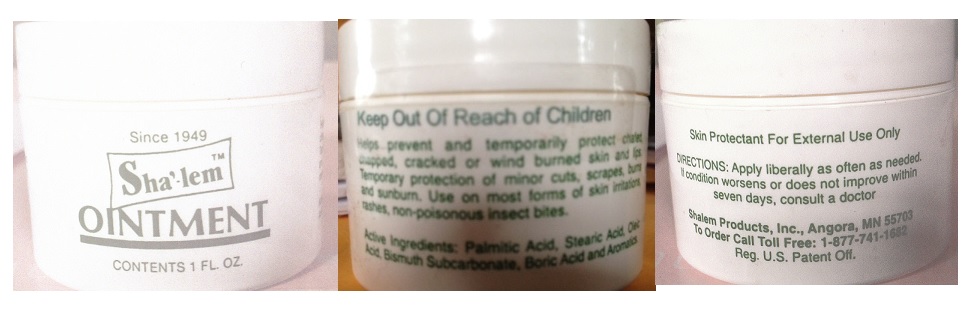 DRUG LABEL: Sha-lem
NDC: 59862-100 | Form: OINTMENT
Manufacturer: Shalem Products, Inc.
Category: otc | Type: HUMAN OTC DRUG LABEL
Date: 20151215

ACTIVE INGREDIENTS: PALMITIC ACID 7.25 g/30 mL; STEARIC ACID 7.25 g/30 mL; OLEIC ACID 14.5 g/30 mL; BISMUTH SUBCARBONATE 1.89 g/30 mL; BORIC ACID 0.95 g/30 mL
INACTIVE INGREDIENTS: WHITE WAX

Sha'-lemTM OINTMENT

Active Ingredients

Palmitic Acid, Stearic Acid, Oleic Acid, Bismuth Subcarbonate, Boric Acid

Purpose

Skin Protectant

Keep Out Of Reach of Children

Uses

Helps prevent and temporarily protects chafed, chapped, cracked or wind burned skin and lips. Temporary protection of minor cuts, scrapes, burns and sunburn. Use on most forms of skin irritations, rashes, non-poisonous insect bites.

Warnings

Skin Protectant For External Use Only

DOSAGE AND ADMINISTRATION

DIRECTIONS: Apply liberally as often as needed. If condition worsens or does not improve within seven days, consult a doctor

Inactive ingredient

White wax

QUESTIONS

To Order Call Toll Free: 1-877-741-1682

Shalem Products, Inc., Angora, MN 55703
Reg. U.S. Patent Off.